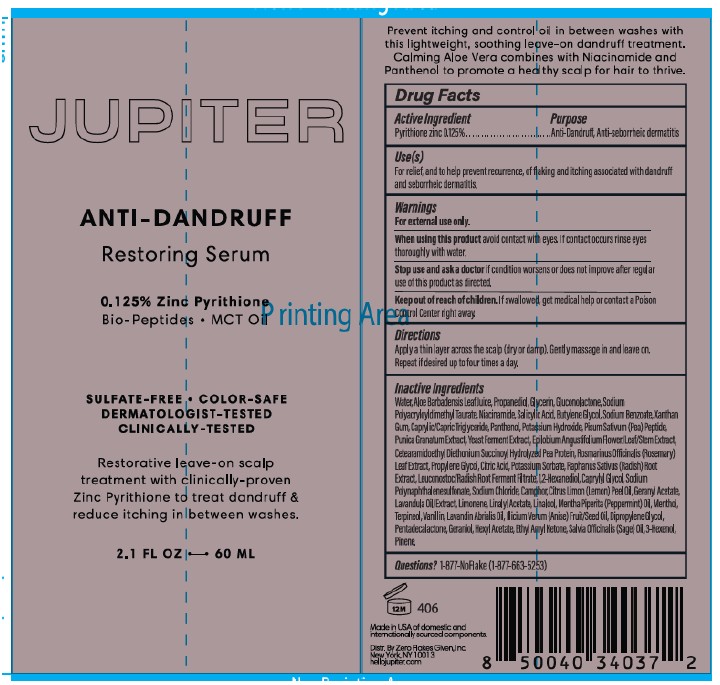 DRUG LABEL: Treatment
NDC: 73528-400 | Form: CREAM
Manufacturer: Zero Flakes Given, Inc.
Category: otc | Type: HUMAN OTC DRUG LABEL
Date: 20250205

ACTIVE INGREDIENTS: PYRITHIONE ZINC 0.125 g/100 mL
INACTIVE INGREDIENTS: WATER; POTASSIUM SORBATE; SODIUM MONO- AND DIMETHYL NAPHTHALENE SULFONATES; SODIUM CHLORIDE; CAPRYLIC/CAPRIC TRIGLYCERIDE; PUNICA GRANATUM FRUIT JUICE; EPILOBIUM ANGUSTIFOLIUM WHOLE; DIPROPYLENE GLYCOL; CITRUS LIMON (LEMON) PEEL OIL; PROPYLENE GLYCOL; HEXYL CINNAMAL; SALICYLIC ACID; XANTHAN GUM; PANTHENOL; CAMPHOR (NATURAL); RAPHANUS SATIVUS VAR. CAUDATUS ROOT; 1,2-HEXANEDIOL; PROPANEDIOL; MENTHOL; SODIUM BENZOATE; PEA PROTEIN; CITRIC ACID; CAPRYLYL GLYCOL; LAVANDULA ANGUSTIFOLIA (LAVENDER) OIL; LINALOOL; MENTHA PIPERITA (PEPPERMINT) OIL; LAVANDIN OIL; TERPINEOL; POTASSIUM HYDROXIDE; GERANYL ACETATE; ALOE BARBADENSIS LEAF JUICE; GLUCONOLACTONE; SODIUM POLYACRYLOYLDIMETHYL TAURATE; NIACINAMIDE; BUTYLENE GLYCOL; PISUM SATIVUM WHOLE; YEAST, UNSPECIFIED; ROSMARINUS OFFICINALIS (ROSEMARY) LEAF OIL; LEUCONOSTOC/RADISH ROOT FERMENT FILTRATE; LINALYL ACETATE; VANILLIN; ILLICIUM VERUM WHOLE; PENTADECALACTONE; 3-OCTANONE; SALVIA OFFICINALIS (SAGE) OIL; 3-HEXENOL; PINENE; GLYCERIN; GERANIOL; LIMONENE, (+/-)-

Restoring Serum (73528-400)

ACTIVE INGREDIENT

Zinc Pyrithione 0.125%

PURPOSE

Anti-Dandruff, Anti-seborrheic dermatitis

INDICATIONS AND USAGE

For the relief of symptoms from scalp itch, irritation, flaking and redness associated with dandruff.

DOSAGE AND ADMINISTRATION

- Apply a thin layer across the scalp (dry or damp). Gently massage into the scalp and leave-on.
- Repeat if desired up to four times a day.
- For best results, use at least twice a week or as directed by a doctor.

WARNINGS

For external use only

WHEN USING

Avoid contact with eyes. If contact occurs rinse eyes thoroughly with water.

Stop use and ask a doctor if condition worsens or does not improve after regular use of this product as directed.

Keep out of reach of children. If swallowed, get medical help or contact a Poison Control Center right away.

INACTIVE INGREDIENT

Aqua (Water, Eau), Aloe Barbadensis Leaf Juice, Propanediol, Glycerin, Gluconolactone, Sodium Polyacryloyldimethyl Taurate, Niacinamide, Salicylic Acid, Butylene Glycol, Sodium Benzoate, Xanthan Gum, Caprylic/Capric Triglyceride, Panthenol, Potassium Hydroxide, Pisum Sativum (Pea) Peptide, Punica Granatum Extract, Yeast Ferment Extract, Epilobium Angustifolium Flower/Leaf/Stem Extract, Cetearamidoethyl Diethonium Succinoyl Hydrolyzed Pea Protein, Rosmarinus Officinalis (Rosemary) Leaf Extract, Propylene Glycol, Citric Acid, Potassium Sorbate, Raphanus Sativus (Radish) Leaf Extract, Leuconostoc/Radish Root Ferment Filtrate, 1,2-Hexanediol, Caprylyl Glycol, Sodium Polynaphthalenesulfonate, Sodium Chloride, Camphor, Citrus Limon (Lemon) Peel Oil, Geranyl Acetate, Lavandula Oil/Extract, Limonene, Linalyl Acetate, Linalool, Mentha Piperitta (Peppermint) Oil, Menthol, Terpineol, Vanillin, Lavandin Abrialis Oil, Illicium Verum (Anise) Fruit/Seed Oil, Dipropylene Glycol, Pentadecalactone, Geraniol, Hexyl Acetate, Ethyl Amyl Ketone, Salvia Officinalis (Sage) Oil, 3-Hexenol, Pinene.

QUESTIONS

1-877-No-Flake (1-877-663-5253)